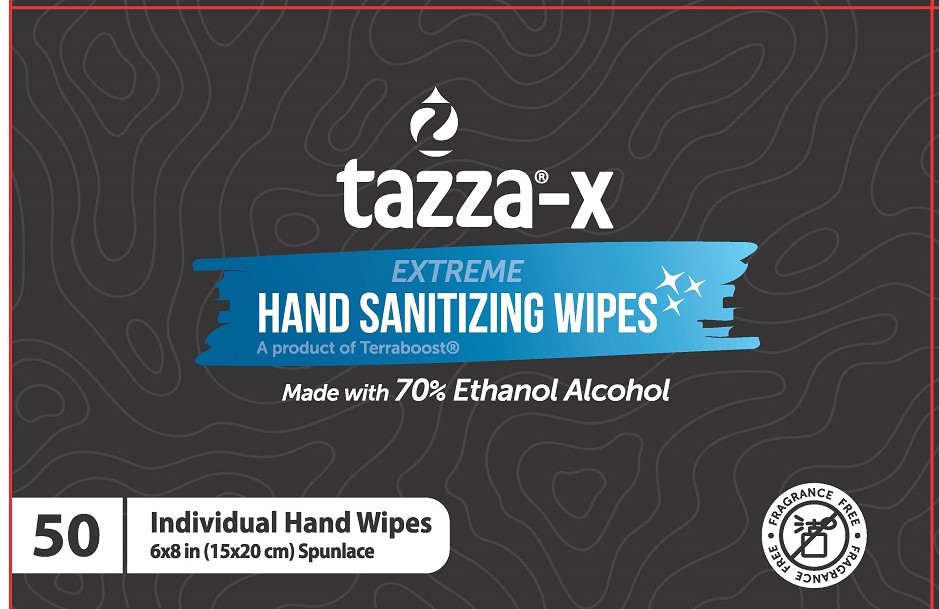 DRUG LABEL: Tazza-X Extreme Hand Sanitizing Wipes
NDC: 76370-0010 | Form: CLOTH
Manufacturer: Tazza Brands East Inc.
Category: otc | Type: HUMAN OTC DRUG LABEL
Date: 20240124

ACTIVE INGREDIENTS: ALCOHOL 70 mL/100 mL
INACTIVE INGREDIENTS: WATER; GLYCERIN; ALOE VERA LEAF; PROPYLENE GLYCOL; DECYL GLUCOSIDE

Tazza-X Extreme Hand Sanitizing Wipes Alcohol Formula

Drug Facts

Active ingredient

Ethyl Alcohol 70%

Purpose

Antiseptic

Uses

- to decrease bacteria on the skin
- recommended for repeated use

Warnings

For external use only

Flammable. Keep away from fire or flame.

When using this product keep away from eyes. In case of eye contact, rinse eyes with water.

Stop use and ask a doctor if irritation or redness develop or last more than 72 hours

Keep out of reach of children. If swallowed, get medical help or contact a Poison Control Center right away.

Directions

- rub wipe thoroughly over all surfaces of both hands
- allow to dry without wiping
- supervise children under 6 years old
- not recommended for infants
- dispose of wipe in trash; do not flush

Other information

- store below 100°F (38°C)

INACTIVE INGREDIENT

Inactive ingredients Aloe Barbadensis Leaf Juice, Decyl Glucoside, Glycerin, Propylene Glycol, Purified Water

Manufactured for Terraboost Media, LLC • 3109 Grand Avenue #300, Miami, FL 33133

A product of Terraboost® • 877-837-7210 • www.tazzabrands.com • Made in China

PACKAGE LABEL

tazza®-X

EXTREME HAND SANITIZING WIPES

A product of Terraboost®

Made with 70% Ethanol Alcohol

50 Individual Hand Wipes

6x8 in (15x20 cm) Spunlace

FRAGRANCE FREE